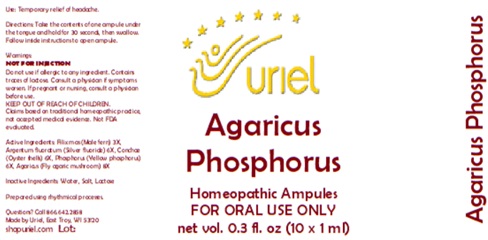 DRUG LABEL: Agaricus Phosphorus
NDC: 48951-1022 | Form: LIQUID
Manufacturer: Uriel Pharmacy Inc.
Category: homeopathic | Type: HUMAN OTC DRUG LABEL
Date: 20251121

ACTIVE INGREDIENTS: DRYOPTERIS FILIX-MAS ROOT 3 [hp_X]/1 mL; SILVER FLUORIDE 6 [hp_X]/1 mL; OSTREA EDULIS SHELL 6 [hp_X]/1 mL; PHOSPHORUS 6 [hp_X]/1 mL; AMANITA MUSCARIA FRUITING BODY 8 [hp_X]/1 mL
INACTIVE INGREDIENTS: SODIUM CHLORIDE; WATER

Agaricus Phosphorus

PURPOSE

Use: Temporary relief of headache.

INDICATIONS AND USAGE

FOR ORAL USE ONLY

DOSAGE AND ADMINISTRATION

Directions: Take the contents of one ampule under the tongue and hold for 30 seconds, then swallow. Follow inside instructions to open ampule.

Warnings:
NOT FOR INJECTION
Do not use if allergic to any ingredient. Contains traces of lactose. Consult a physician if symptoms worsen. If pregnant or nursing, consult a physician before use.
Claims based on traditional homeopathic practice, not accepted medical evidence. Not FDA evaluated.

KEEP OUT OF REACH OF CHILDREN.

ACTIVE INGREDIENT

Active Ingredients: Filix mas (Male fern) 3X, Argentum fluoratum (Silver fluoride) 6X, Conchae (Oyster shells) 6X, Phosphorus (Yellow phosphorus) 6X, Agaricus (Fly agaric mushroom) 8X

Inactive Ingredients: Water, Salt, Lactose

Prepared using rhythmical processes.

QUESTIONS

Questions? Call 866.642.2858 Made by Uriel, East Troy, WI 53120 shopuriel.com Lot: